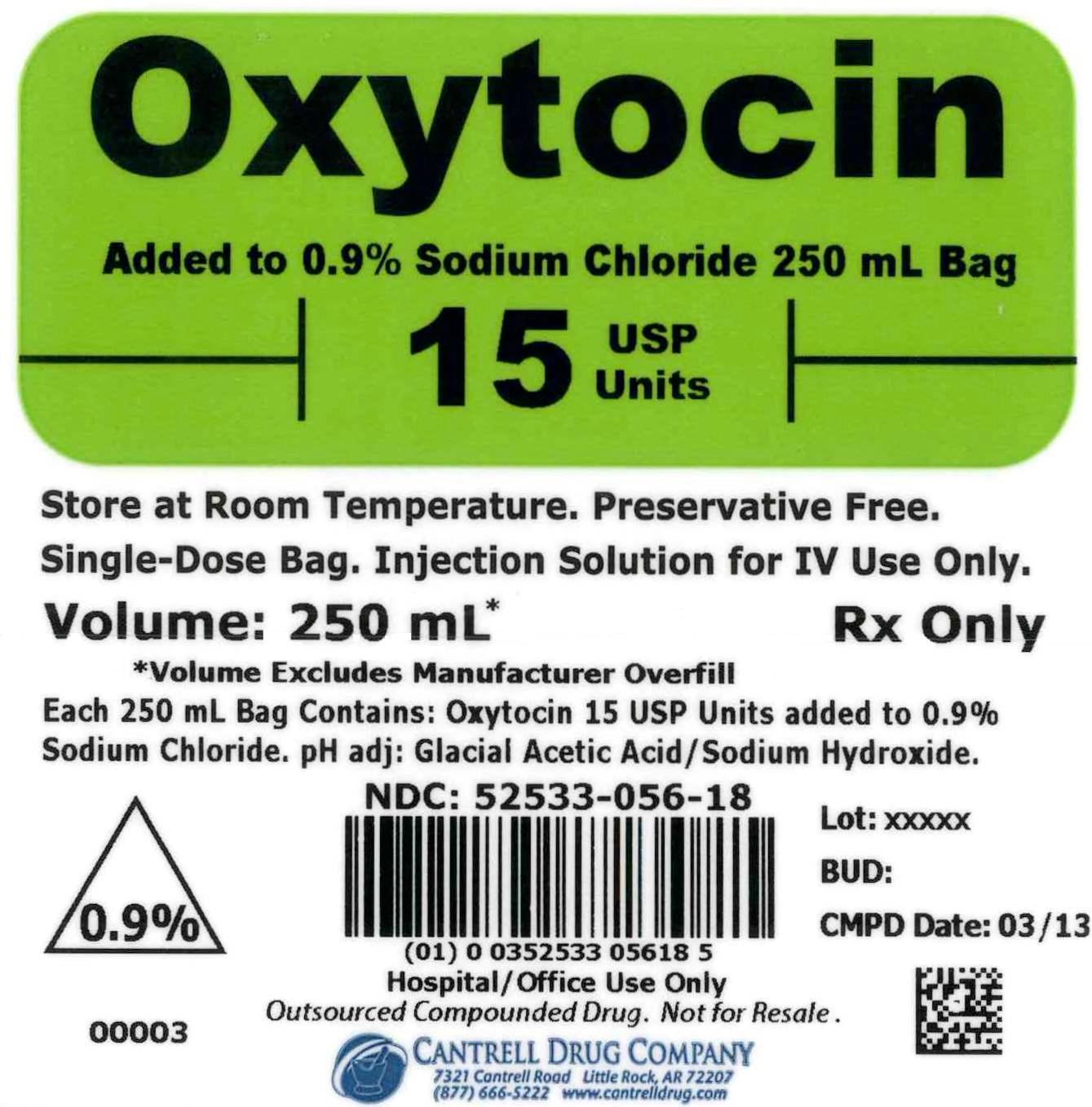 DRUG LABEL: Oxytocin
NDC: 52533-056 | Form: INJECTION, SOLUTION
Manufacturer: Cantrell Drug Company
Category: prescription | Type: HUMAN PRESCRIPTION DRUG LABEL
Date: 20141211

ACTIVE INGREDIENTS: OXYTOCIN 15 [USP'U]/250 mL
INACTIVE INGREDIENTS: Sodium Chloride 2.25 g/250 mL; Water

Oxytocin 15 USP Units Added to 0.9% Sodium Chloride 250 mL Bag